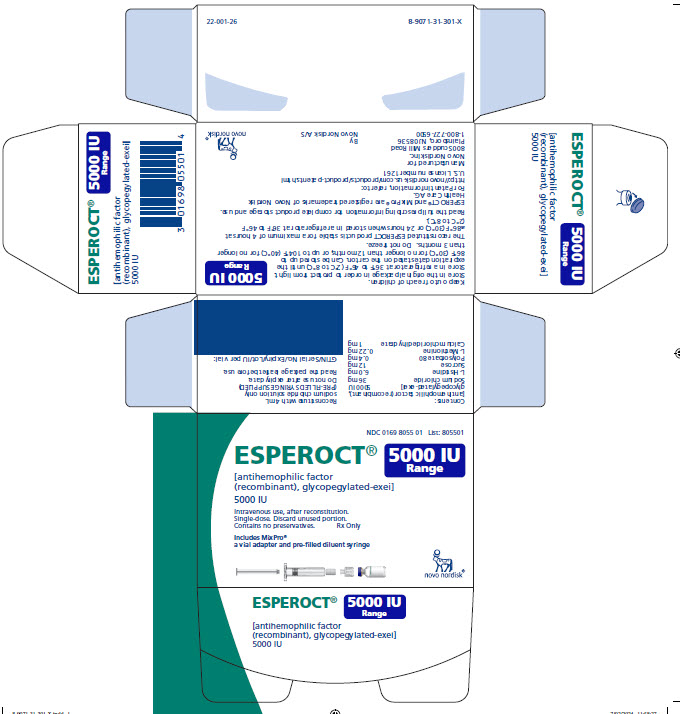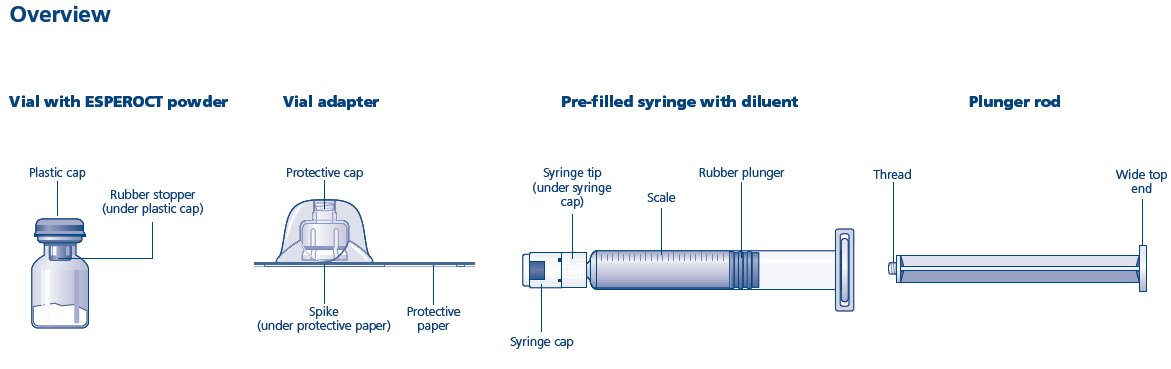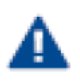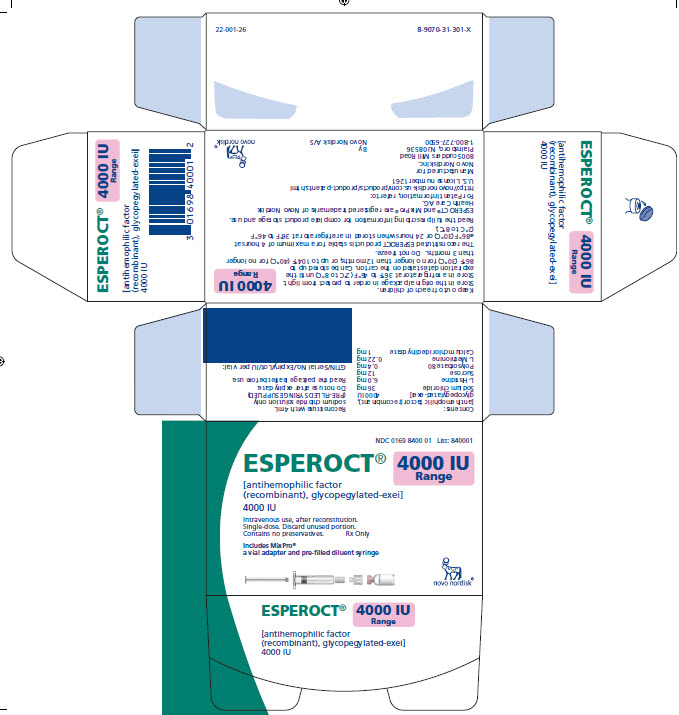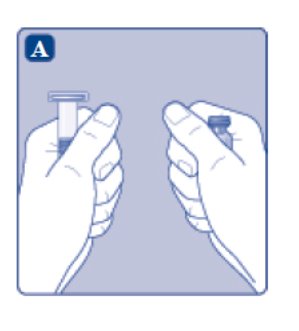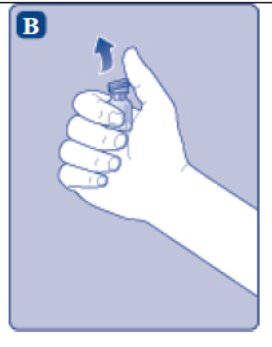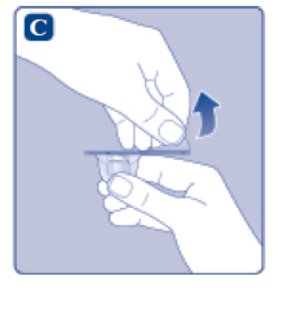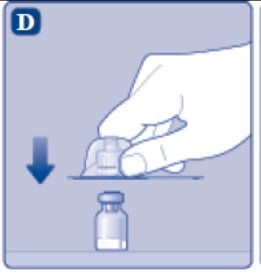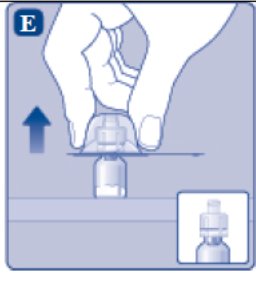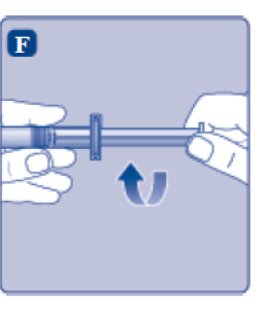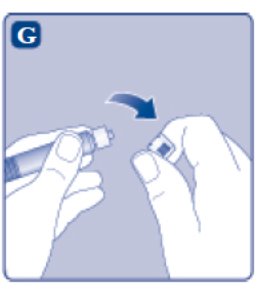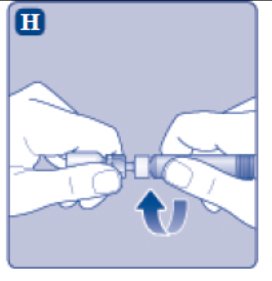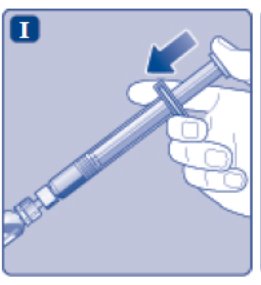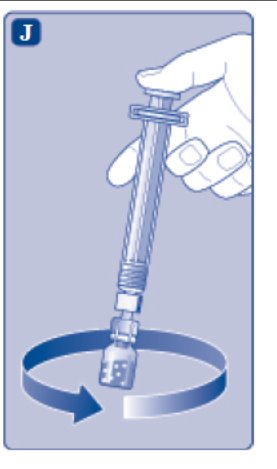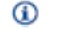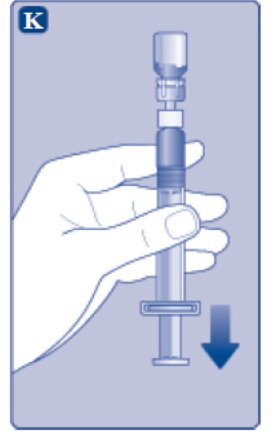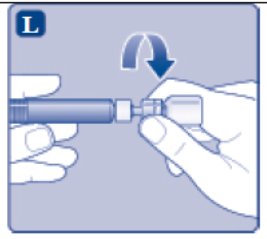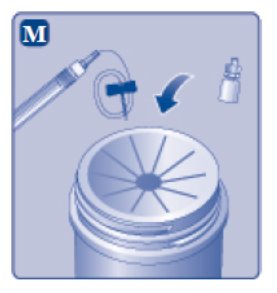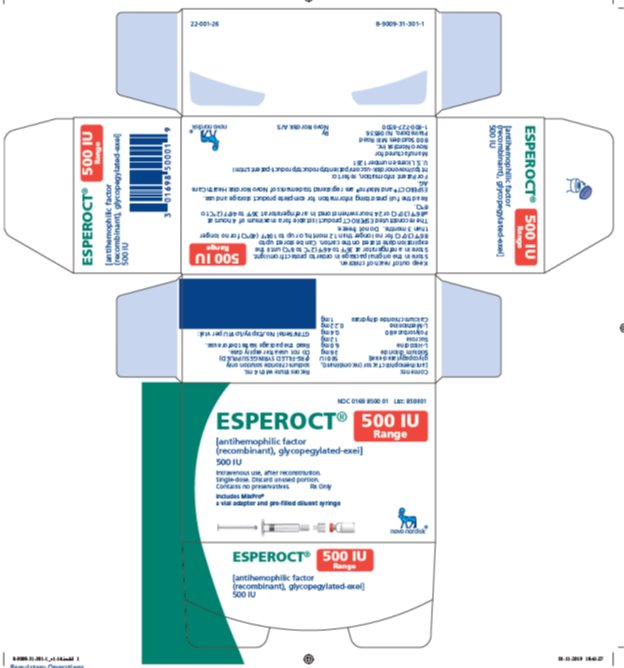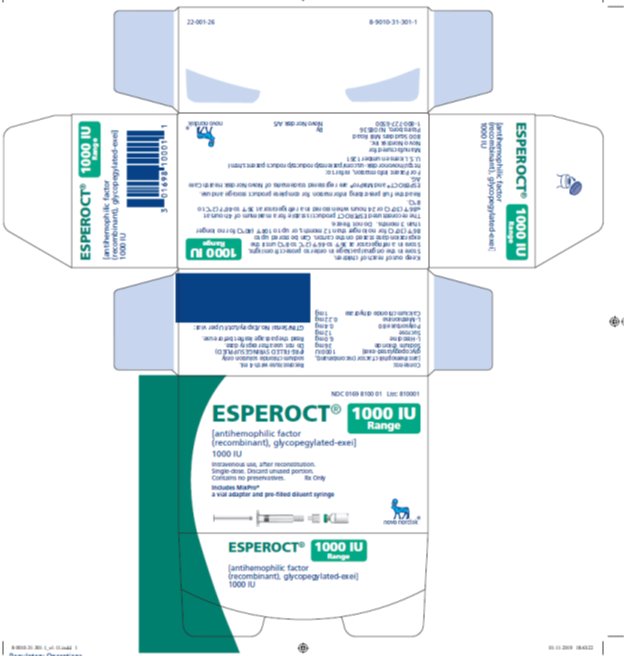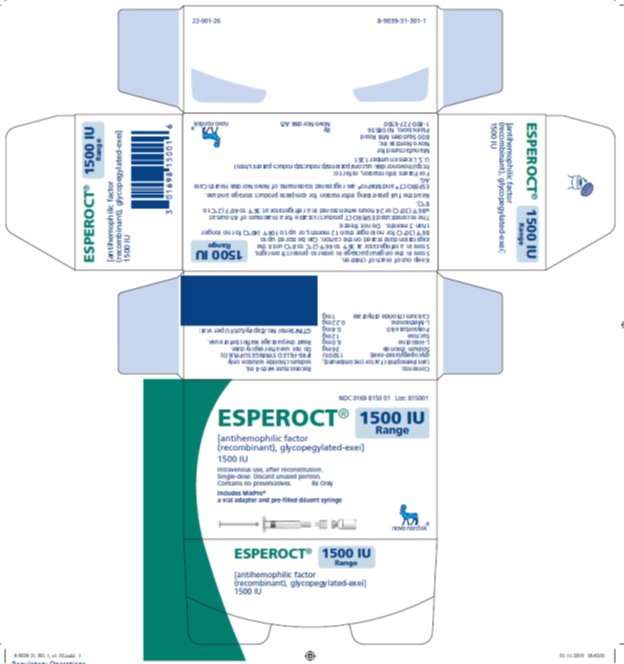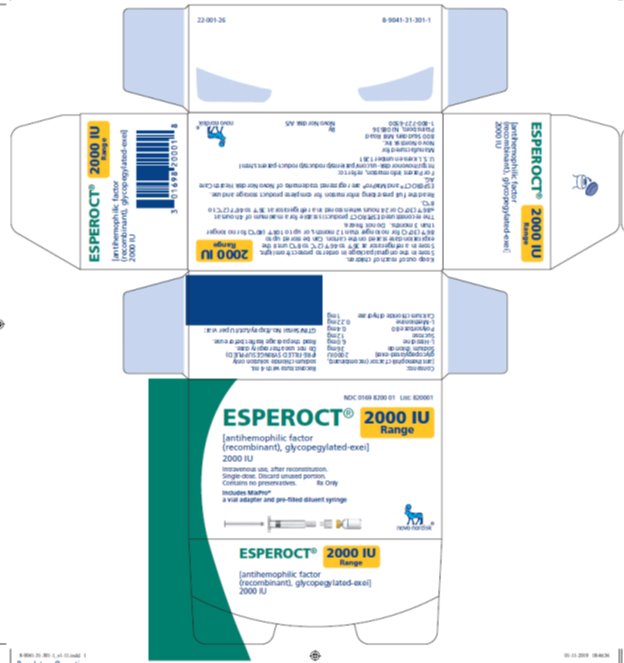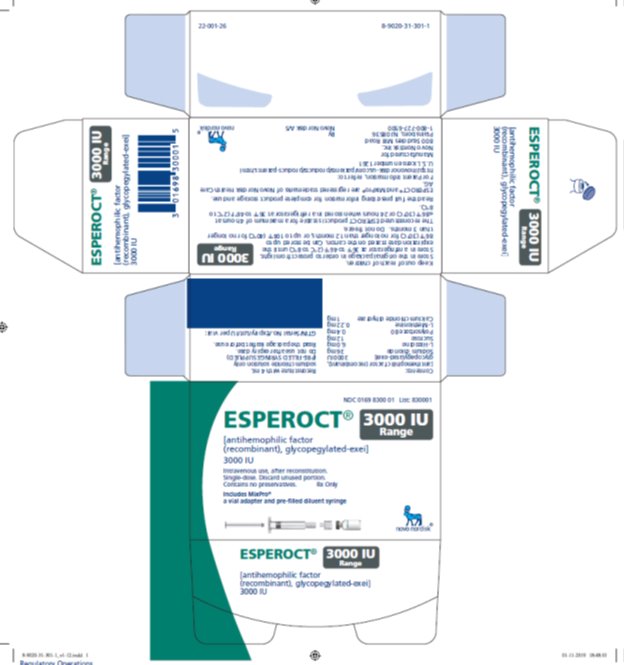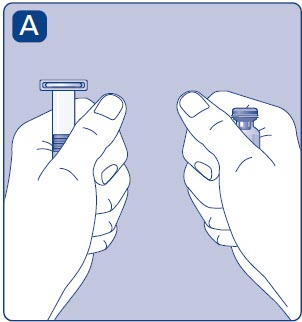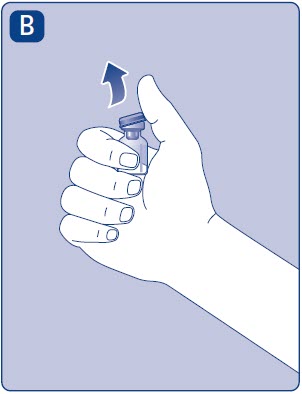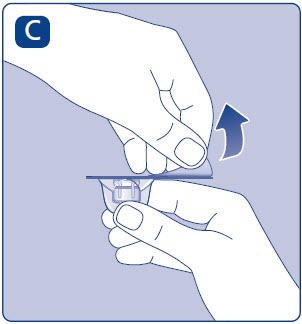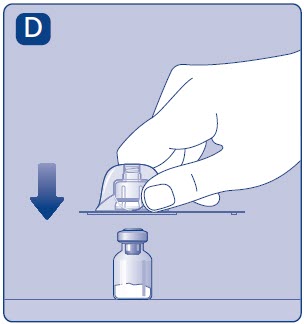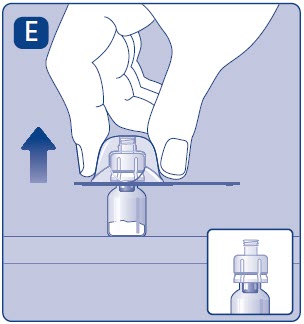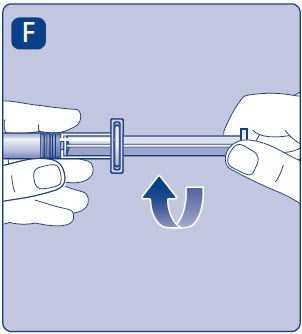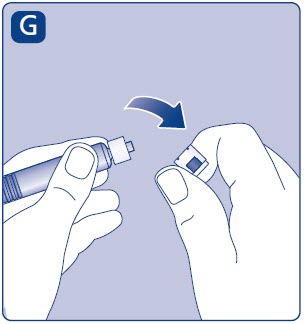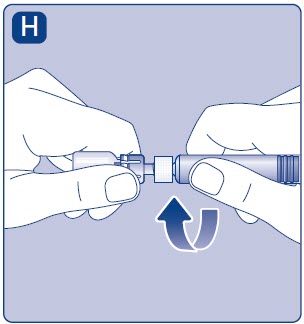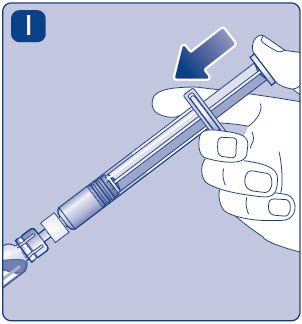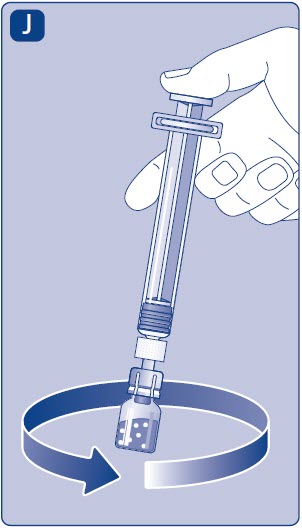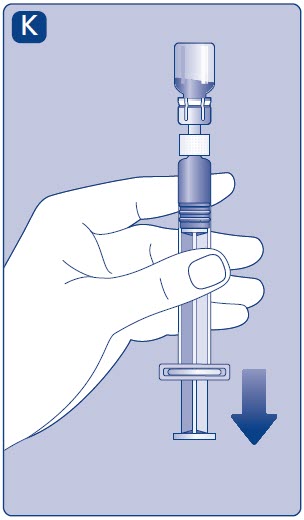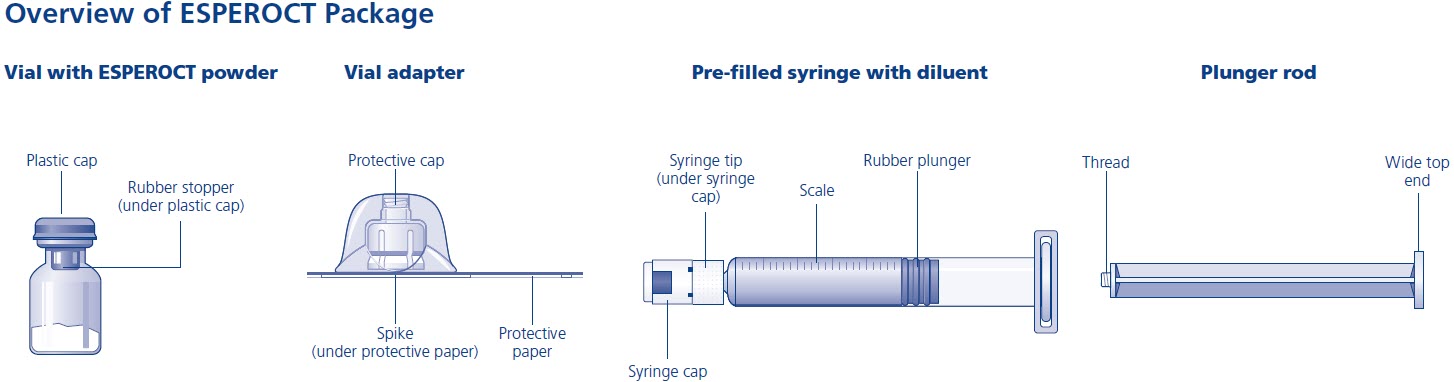 DRUG LABEL: ESPEROCT
NDC: 0169-8500 | Form: KIT | Route: INTRAVENOUS
Manufacturer: Novo Nordisk
Category: other | Type: PLASMA DERIVATIVE
Date: 20240701

ACTIVE INGREDIENTS: ANTIHEMOPHILIC FACTOR, HUMAN RECOMBINANT 125 [iU]/1 mL
INACTIVE INGREDIENTS: SODIUM CHLORIDE; HISTIDINE; SUCROSE; POLYSORBATE 80; METHIONINE; CALCIUM CHLORIDE; SODIUM CHLORIDE

HIGHLIGHTS OF PRESCRIBING INFORMATION

These highlights do not include all the information needed to use ESPEROCT® safely and effectively. See full prescribing information for ESPEROCT.
ESPEROCT [antihemophilic factor (recombinant),
glycopegylated-exei]
lyophilized powder for solution, for intravenous use
Initial U.S. Approval: 2019

RECENT MAJOR CHANGES

Warnings and Precautions (5.3) …………………………….02/2024

1 INDICATIONS AND USAGE

ESPEROCT [antihemophilic factor (recombinant), glycopegylated-exei] is a coagulation Factor VIII concentrate indicated for use in adults and children with hemophilia A for:

- On-demand treatment and control of bleeding episodes
- Perioperative management of bleeding
- Routine prophylaxis to reduce the frequency of bleeding episodes (1)

Limitation of Use

ESPEROCT is not indicated for the treatment of von Willebrand disease. (1)

2 DOSAGE AND ADMINISTRATION

For intravenous infusion after reconstitution only.

- Each vial label for ESPEROCT states the actual Factor VIII activity in international units (IU). (2.1)
- On-demand treatment/control of bleeding episodes: In adolescents / adults, 40 IU/kg body weight for minor/moderate bleeds and 50 IU/kg body weight for major bleeds; children (<12 years), 65 IU/kg body weight for minor/moderate/major bleeds. (2.1)
- Perioperative management: For minor/major surgery: In adolescents / adults: pre-operative dose of 50 IU/kg body weight; in children (<12 years), pre-operative dose of 65 IU/kg body weight. Frequency of administration is determined by the treating physician. (2.1)
- Routine prophylaxis: In adolescents/adults, 50 IU/kg every 4 days; in children (<12 years), 65 IU/kg twice weekly. A regimen may be individually adjusted to less or more frequent dosing based on bleeding episodes. (2.1)
- ESPEROCT also may be dosed to achieve a specific target Factor VIII activity level, depending on the severity of hemophilia, for on-demand treatment/control of bleeding episodes or perioperative management. To achieve a specific target Factor VIII activity level, use the following formula:
Dosage (IU) = Body Weight (kg) x Desired Factor VIII Increase (IU/dL or % normal) x 0.5 (IU/kg per IU/dL). (2.1)

3 DOSAGE FORMS AND STRENGTHS

ESPEROCT is available as a lyophilized powder in single-dose vials of dosage strengths at 500, 1000, 1500, 2000, 3000, 4000, and 5000 IU per vial. (3)

4 CONTRAINDICATIONS

Do not use in patients who have known hypersensitivity to ESPEROCT or its components, including hamster proteins. (4)

5 WARNINGS AND PRECAUTIONS

- Hypersensitivity reactions, including anaphylaxis, may occur. If a hypersensitivity reaction occurs, discontinue ESPEROCT and administer appropriate treatment. (5.1)
- Development of neutralizing antibodies (inhibitors) has occurred. If bleeding is not controlled with the recommended dose of ESPEROCT, or if the expected plasma Factor VIII activity levels are not attained, then perform an assay that measures Factor VIII inhibitor concentration. (5.2, 5.4)
- Temporary decrease in Factor VIII incremental recovery has been observed after ESPEROCT infusion in previously untreated pediatric patients (PUPs). (5.3)

6 ADVERSE REACTIONS

The most frequently reported adverse reactions (≥ 1%) were rash, redness, itching and injection site reactions. (6)

Additional frequently reported adverse reactions (≥ 1%) in PUPs included Factor VIII inhibition and hypersensitivity. (6)

To report SUSPECTED ADVERSE REACTIONS, contact Novo Nordisk Inc. at 1-800-727-6500 or FDA at 1-800-FDA-1088 or www.fda.gov/medwatch.

8 USE IN SPECIFIC POPULATIONS

Pediatric Use: Higher clearance (based on kg body weight), a shorter half-life and lower incremental recovery are seen in children. Higher and more frequent dosing may be needed. (8.4)

FULL PRESCRIBING INFORMATION

1 INDICATIONS AND USAGE

ESPEROCT [antihemophilic factor (recombinant), glycopegylated-exei] is a recombinant DNA-derived coagulation Factor VIII concentrate indicated for use in adults and children with hemophilia A for:

- On-demand treatment and control of bleeding episodes
- Perioperative management of bleeding
- Routine prophylaxis to reduce the frequency of bleeding episodes

Limitation of Use:

ESPEROCT is not indicated for the treatment of von Willebrand disease.

2 DOSAGE AND ADMINISTRATION

For intravenous infusion after reconstitution only.

2.1 Dose

- Dosage and duration of treatment depend on the severity of the Factor VIII deficiency, on the location and extent of bleeding, and on the patient’s clinical condition. Careful monitoring of replacement therapy is necessary in cases of major surgery or life-threatening bleeding episodes.
- Each vial of ESPEROCT contains the labeled amount of recombinant Factor VIII in international units (IU). One IU of Factor VIII activity corresponds to the quantity of Factor VIII in one milliliter of normal human plasma. The calculation of the required dosage of Factor VIII is based on the empirical finding that one IU of Factor VIII per kg body weight raises the plasma Factor VIII activity by two IU/dL.

On–demand Treatment and Control of Bleeding Episodes

Table 1 can be used to guide dosing of ESPEROCT for treatment of bleeding episodes.

Table 1: Dosing of ESPEROCT to Control Bleeding Episodes

Type of bleeding | Adolescents/Adults ≥12 years Dose (IU/kg) | Children <12 years Dose (IU/kg) | Additional doses
Minor; Early hemarthrosis, mild muscle bleeding, or oral bleeding | 40 | 65 | One dose should be sufficient
Moderate; More extensive hemarthrosis, muscle bleeding, or hematoma | 40 | 65 | An additional dose may be administered after 24 hours
Major; Life- or limb-threatening hemorrhages, gastro- intestinal bleeding, intracranial, intra-abdominal or intrathoracic bleeding, fractures | 50 | 65 | Additional dose(s) may be administered approximately every 24 hours

Perioperative Management

The dose level and dosing intervals for surgery depend on the procedure and local practice. A guide for dosing with ESPEROCT during surgery (perioperative management) is provided in Table 2 below.

Table 2: Dosing for Perioperative Management with ESPEROCT

Type of surgery | Adolescents/Adults; ≥12 years; Pre-operative Dose (IU/kg) | Children; <12 years; Pre-operative Dose (IU/kg) | Additional Doses
Minor; Including tooth extraction | 50 | 65 | Additional dose(s) can be administered after 24 hours if necessary
Major; Intracranial,; intra-abdominal, intrathoracic, or joint replacement surgery | 50 | 65 | Additional doses can be administered approximately every 24 hours for the first week and then approximately every 48 hours until wound healing has occurred

Routine Prophylaxis

Adults and adolescents (≥ 12 years): The recommended starting dose is 50 IU of ESPEROCT per kg body weight every 4 days. This regimen may be individually adjusted to less or more frequent dosing based on bleeding episodes.

Children (< 12 years): A dose of 65 IU of ESPEROCT per kg body weight twice weekly. This regimen may be individually adjusted to less or more frequent dosing based on bleeding episodes.

- ESPEROCT also may be dosed to achieve a specific target Factor VIII activity level, depending on the severity of hemophilia, for on-demand treatment/control of bleeding episodes or perioperative management. To achieve a specific target Factor VIII activity level, use the following formula:
Dosage (IU) = Body Weight (kg) × Desired Factor VIII Increase (IU/dL or % normal) × 0.5
- Base the dose and frequency of ESPEROCT on the individual clinical response. Patients may vary in their pharmacokinetic and clinical responses.
- If monitoring of Factor VIII activity is performed, use a chromogenic or one-stage clotting assay appropriate for use with ESPEROCT [see Warnings and Precautions (5.3)].

2.2 Preparation and Reconstitution

- Always wash hands and ensure that the area is clean before performing the reconstitution procedures.
- Use aseptic technique during the reconstitution procedures.
- If the dose requires more than one vial of ESPEROCT per infusion, reconstitute each vial according to the following instructions.

Reconstitution

1. Bring the ESPEROCT vial and the pre-filled diluent syringe to room temperature.

2. Remove the plastic cap from the ESPEROCT vial.

3. Wipe the rubber stopper on the vial with a sterile alcohol swab and allow it to dry prior to use.
4. Remove the protective paper from the vial adapter. Do not remove the vial adapter from the protective cap.

5. Place the ESPEROCT vial on a flat and solid surface. While holding the protective cap, place the vial adapter over the ESPEROCT vial and press down firmly on the protective cap until the vial adapter spike penetrates the rubber stopper.

6. Carefully remove the protective cap from the vial adapter.

7. Grasp the plunger rod as shown in the diagram. Attach the plunger rod to the syringe by holding the plunger rod by the wide top end. Turn the plunger rod clockwise into the rubber plunger inside the pre-filled diluent syringe until resistance is felt.

8. Break off the syringe cap from the pre-filled diluent syringe by snapping the perforation of the cap.

9. Connect the pre-filled diluent syringe to the vial adapter by turning it clockwise until it is secured.

10. Push the plunger rod to slowly inject all the diluent into the vial.

11. Without removing the syringe, gently swirl the ESPEROCT vial until all of the powder is dissolved. Avoid shaking the vial and foaming the solution.

2.3 Administration

For intravenous infusion only.

- Parenteral drug products should be inspected visually for particulate matter and discoloration prior to administration, whenever solution and container permit. The solution should be clear and have no particles. Do not use if particulate matter or discoloration is observed.
- Do not administer ESPEROCT in the same tubing or container with other medicinal products.
- Administer the ESPEROCT solution immediately. If not, store the solution in the vial with the vial adapter and the syringe attached. Use ESPEROCT within 4 hours when stored at ≤86°F (30°C) or within 24 hours when stored in a refrigerator at 36°F to 46°F (2°C to 8°C).
1. Invert the ESPEROCT vial and slowly draw the solution into the syringe.

2. Detach the syringe from the vial adapter by turning the syringe counterclockwise.
3. Attach the syringe to the luer end of an infusion needle set.
4. Infuse the reconstituted ESPEROCT intravenously slowly over approximately 2 minutes.
5. After infusion, safely dispose of the syringe with the infusion set, the vial with the vial adapter, any unused ESPEROCT, and other waste materials.

Caution: The pre-filled diluent syringe is made of glass with an internal tip diameter of 0.037 inches and is compatible with a standard Luer-lock connector.

Some needleless connectors for intravenous catheters are incompatible with the glass diluent syringes (for example, certain connectors with an internal spike, such as Clave®/MicroClave®, InVision-Plus®, InVision-Plus CS®, Invision-Plus Junior®, Bionector®), and their use can damage the connector and affect administration. To administer ESPEROCT through incompatible needleless connectors, withdraw the reconstituted product into a standard 10 mL sterile Luer-lock plastic syringe.

3 DOSAGE FORMS AND STRENGTHS

ESPEROCT is available as a sterile white to off-white lyophilized powder supplied in single-dose vials containing nominally 500, 1000, 1500, 2000, 3000, 4000, or 5000 IU. The actual FVIII activity is printed on each ESPEROCT vial and carton.

After reconstitution with 4 mL of saline diluent, the reconstituted solution contains approximately 125, 250, 375, 500, 750, 1000, or 1250 IU per mL of ESPEROCT, respectively.

4 CONTRAINDICATIONS

ESPEROCT is contraindicated in patients who have known hypersensitivity to ESPEROCT or its components (including hamster proteins) [see Warnings and Precautions (5.1) and Description (11)].

5 WARNINGS AND PRECAUTIONS

5.1 Hypersensitivity Reactions

Allergic-type hypersensitivity reactions, including anaphylaxis, are possible with ESPEROCT. The product contains traces of hamster proteins, which in some patients may cause allergic reactions [see Description (11)]. Early signs of allergic reactions, which can progress to anaphylaxis, may include angioedema, chest tightness, difficulty breathing, wheezing, rash, hives, and itching. Observe patients for signs and symptoms of acute hypersensitivity reactions, particularly during the early phases of exposure to the product. Discontinue use of ESPEROCT if allergic- or anaphylactic-type reactions occur, and initiate appropriate treatment.

5.2 Neutralizing Antibodies

The formation of neutralizing antibodies (inhibitors) to Factor VIII has occurred following administration of ESPEROCT. Monitor patients for the development of Factor VIII inhibitors by appropriate clinical observations and laboratory tests. If expected Factor VIII activity plasma levels are not attained, or if bleeding is not controlled after ESPEROCT administration, suspect the presence of an inhibitor (neutralizing antibody) [see Warnings and Precautions (5.3)].

5.3 Decreased Incremental Recovery in Previously Untreated Patients

Incremental recovery (IR) is defined as the increase in plasma Factor VIII activity per IU/kg of ESPEROCT. Decreased IR, defined as having at least 2 consecutive observations of low IR values (<0.6 (IU/dL)/(IU/kg) after treatment with ESPEROCT, was observed in a trial of PUPs <6 years of age within the first 5 exposure days (ED) to ESPEROCT. Decreased IR was observed in 17 out of 59 (28.8%) subjects without factor VIII inhibition. This may be associated with high titers of anti-PEG binding antibodies. Decreased IR was temporary and returned to ≥ 0.6 (IU/dL)/(IU/kg) between 15 to 70 EDs if ESPEROCT was continued.

As part of a post hoc subgroup analysis, the bleeding tendency was evaluated in the 17 subjects who experienced a temporary decreased IR. The mean treatment duration was 0.48 years, after which IR normalized in subjects continuing treatment (N=13). During the period of decreased IR, 14 out of 17 subjects experienced a total of 30 bleeds while on prophylaxis, of which 7 (23.3 %) were spontaneous. For non-inhibitor, non-decreased IR subjects, 36 (18.1%) of the total 199 bleeding episodes (mean treatment duration of 3.71 years) were reported as spontaneous. Subjects with decreased IR may have an increased bleeding tendency during the decreased IR period [see Adverse Reactions (6.2)].

If bleeding is not controlled with the recommended dose of ESPEROCT and/or the expected Factor VIII activity levels in the plasma are not attained and Factor VIII inhibitors are not detected, consider adjusting the dose, dosing frequency or discontinuing the product.

5.4 Monitoring Laboratory Tests

If monitoring of Factor VIII is performed, use a chromogenic or one-stage clotting assay appropriate for use with ESPEROCT [see Dosage and Administration (2)].

Factor VIII activity levels can be affected by the type of activated partial thromboplastin time (aPTT) reagent used in the assay. Some silica-based aPTT reagents can underestimate the activity of ESPEROCT by up to 60%; other reagents may overestimate the activity by 20%. If an appropriate one-stage clotting or chromogenic assay is not available locally, then use a reference laboratory.

If bleeding is not controlled with the recommended dose of ESPEROCT or if the expected Factor VIII activity levels in plasma are not attained, then perform a Bethesda assay to determine if Factor VIII inhibitors are present.

6 ADVERSE REACTIONS

The most frequently reported adverse reactions (incidence ≥1%) in previously treated patients (PTPs) and previously untreated patients (PUPs) in clinical trials were rash, redness, itching (pruritus), and injection site reactions. Additional frequently reported adverse reactions (incidence ≥1%) in PUPs included Factor VIII inhibition (30%), and drug hypersensitivity (2.5%).

6.1 Clinical Trials Experience

Because clinical trials are conducted under widely varying conditions, adverse reaction rates observed in the clinical trials of a drug cannot be directly compared to rates in clinical trials of another drug and may not reflect the rates observed in clinical practice.

The safety of ESPEROCT has been evaluated in 270 subjects (202 adolescents/adults and 68 children) in five prospective, multi-center clinical studies in previously treated patients (PTPs) and 81 subjects (< 6 years of age) in one open-label, multi-center clinical study in previously untreated patients (PUPs) with severe hemophilia A (<1% endogenous Factor VIII activity) and no history of inhibitors. All subjects received at least one dose of ESPEROCT. A previously treated patient was defined as a subject with a history of at least 150 exposure days to other Factor VIII products (adolescent/adult subjects) or 50 exposure days to other Factor VIII products (pediatric subjects). A previously untreated patient was defined as a subject with a diagnosis of severe hemophilia A (FVIII activity level < 1%) based on medical records or central laboratory results with no prior use of purified Factor VIII containing clotting products (5 previous exposure days to blood components are acceptable). Total exposure of PTPs and PUPs to ESPEROCT was 80,425 exposure days corresponding to 889 patient years of treatment and 18,184 exposure days corresponding to 234 patient years of treatment, respectively.

During the clinical trials in PTPs, adverse reactions occurred at a rate of 0.10 events per patient year of exposure. The most frequently reported adverse reactions were rash (5.2%), injection site reaction (2.6%), redness (1.9%), and itching (pruritus) (1.5%).

During the clinical trial in PUPs, adverse reactions occurred at a rate of 0.25 events per patient year of exposure. The most frequently reported adverse reactions were Factor VIII inhibition (30%), injection site reaction (2.5%), drug hypersensitivity (2.5%), redness (1.2%), and rash (1.2%).

6.2 Immunogenicity

In clinical trials with PTPs and PUPs, subjects were monitored for neutralizing antibodies to Factor VIII (Factor VIII inhibitor), and binding antibodies to Factor VIII or ESPEROCT, polyethylene glycol (PEG), or Chinese hamster ovary (CHO) host cell protein. Table 3 summarizes the number of subjects with anti-drug antibodies in PTPs and PUPs.

Previously treated patients (PTPs)

Of the 270 subjects in the PTP trials, 1 (0.4%) subject developed confirmed neutralizing antibodies to Factor VIII (13.5 Bethesda Units). In addition, 2 (0.7%) subjects had transient low titer FVIII antibody (<5 Bethesda Units) test results at a single occasion. Anti-PEG antibodies of no clinical consequence were detected in 43 (15.9%) PTPs, 32 (11.9%) of whom had pre-existing anti-PEG antibodies. Nine (3.3%) subjects developed anti-CHO host cell protein antibodies of no clinical consequence [see Warnings and Precautions (5.2)].

Previously untreated patients (PUPs)

In a clinical trial in PUPs < 6 years of age, of the 80 treated subjects (excluding 1 subject with pre-existing Factor VIII inhibitors), 21 (26.3%) subjects developed Factor VIII inhibitors (≥ 0.6 Bethesda Units). Of 70 subjects with at least 10 exposure days to ESPEROCT or previously confirmed Factor VIII inhibitors, 21 (30%) subjects developed inhibitors, 11 (15.7%) of whom developed high titer inhibitors (≥ 5 Bethesda Units) and 10 (14.3%) of whom developed low titer inhibitors (< 5 Bethesda Units). Of total 21 subjects with inhibitors, two (2) subjects with high-titer FVIII inhibitor discontinued the trial. Six (6) of the remaining subjects (3 with high-titer and 3 with low-titer) were switched to immune tolerance induction therapy and completed the treatment. Two (2) subjects with high-titer inhibitor remained inhibitor positive until the end of the trial [see Warnings and Precautions (5.2)].

Of the 80 treated subjects, binding antibodies to Factor VIII or ESPEROCT, anti-PEG IgM, anti-PEG IgG, and anti-CHO host cell protein antibodies were developed in 42 (52.5%), 22 (27.5%), 50 (62.5%), and 7 (8.8%) subjects, respectively, except subjects who had pre-existing antibodies. Higher incidence of non-neutralizing antibodies binding to Factor VIII or ESPEROCT was observed in subjects with FVIII inhibitors (20/21, 95.2%) compared to subjects without inhibitors (22/59, 37.3%) whereas the development of anti-PEG IgM and IgG antibodies was not significantly different between inhibitor and non-inhibitor subjects.

Table 3: Incidences of anti-drug antibodies in PTPs and PUPs

 | PTP (all age) (N=270) n (%) | PUP (< 6 years of age) (N=80) n (%)
FVIII neutralizing antibodies
Confirmed inhibitor (≥ 0.6 BU) | 1 (0.4) | 21 (26.3)
High titer inhibitor (≥ 5 BU) | 1 (0.4) | 11 (13.8)
Low titer inhibitor (< 5 BU) | 0 | 10 (12.5)
Anti-ESPEROCT/FVIII binding antibodies
Conversion to positive antibodies | 4 (1.5) | 42 (52.5)
Pre-existing antibodies | 2 (0.7) | 1 (1.3)
Anti-PEG IgM antibodies
Conversion to positive antibodies | 11 (4.1) | 22 (27.5)
Pre-existing antibodies | 32 (11.9) | 16 (20)
Anti-PEG IgG antibodies
Conversion to positive antibodies | NA | 50 (62.5)
Pre-existing antibodies | NA | 14 (17.5)
Anti-CHO host cell protein antibodies
Conversion to positive antibodies | 9 (3.3) | 7 (8.8)
Pre-existing antibodies | 2 (0.7) | 2 (2.5)

Note: “Conversion to positive antibodies” refers only to patients who were not detected with positive antibodies at baseline but developed antibodies post-baseline. “Pre-existing antibodies” refers to patients who were detected with positive antibodies at baseline.
NA: Not analyzed

In PUPs, high titers of anti-PEG IgG antibodies were associated with low Factor VIII incremental recovery (IR). In the PUP trial, a decreased Factor VIII IR, defined as at least 2 consecutive measurements of <0.6 (IU/dL)/(IU/kg) at 30 min post-dose, was identified after exposure to ESPEROCT (5 EDs) in 17 out of 59 (28.8%) subjects without detectable Factor VIII inhibitors, which was observed with increased titers of anti-PEG IgG antibodies. As treatment of ESPEROCT was continued, titers of anti-PEG IgG decreased and IR returned to ≥ 0.6 (IU/dL)/(IU/kg) between 15 to 70 EDs to ESPEROCT. A post hoc subgroup analysis indicated that subjects with decreased IR may have an increased bleeding tendency during the decreased IR period [see Warnings and Precautions (5.3)].

The detection of antibodies is highly dependent on the sensitivity and specificity of the assay. Additionally, the observed incidence of antibody (including neutralizing antibody) positivity in an assay may be influenced by several factors, including assay methodology, sample handling, timing of sample collection, concomitant medications, and underlying disease.

6.3 Postmarketing Experience

The following adverse reactions have been identified during post-approval of ESPEROCT. Because these reactions are reported voluntarily from a population of uncertain size, it is not always possible to reliably estimate their frequency or establish a causal relationship to drug exposure.

Decreased Factor VIII activity: There have been reports of decreased Factor VIII activity in the absence of detectable Factor VIII inhibitors in previously treated patients (PTPs) upon switching to ESPEROCT from other Factor VIII products.

8 USE IN SPECIFIC POPULATIONS

8.1 Pregnancy

Risk Summary

There are no data with ESPEROCT use in pregnant women to determine whether there is a drug-associated risk. Animal reproduction studies have not been conducted with ESPEROCT. It is unknown whether ESPEROCT can cause fetal harm when administered to a pregnant woman or can affect fertility.

In the U.S. general population, the estimated background risk of major birth defect and miscarriage in clinically recognized pregnancies is 2–4% and 15–20%, respectively.

8.2 Lactation

Risk Summary

There is no information regarding the presence of ESPEROCT in human milk, the effect on the breastfed infant, and the effects on milk production. The developmental and health benefits of breastfeeding should be considered along with the mother’s clinical need for ESPEROCT and any potential adverse effects on the breastfed infant from ESPEROCT or from the underlying maternal condition.

8.4 Pediatric Use

The safety and effectiveness of ESPEROCT have been established for pediatric patients for the treatment and control of bleeding episodes, perioperative management, and routine prophylaxis use.

Safety and efficacy were evaluated in 93 PTPs <18 years of age [see Adverse Reactions (6) and Clinical Studies (14)]. Of the PTPs, 34 (36.6%) were 1 to <6 years of age; 34 (36.6%) were 6 to <12 years of age; and 25 (27%) were 12 to <18 years of age. Pharmacokinetic parameters were evaluated for 27 PTPs who were treated with ESPEROCT [see Clinical Pharmacology (12.3)].

No difference in the safety profile of ESPEROCT was observed between previously treated pediatric subjects and adult subjects. Pharmacokinetic studies in children <12 years of age demonstrated higher clearance, a shorter half-life, and lower incremental recovery of Factor VIII compared to adults, but the pharmacokinetic parameters are comparable between young children (1–<6 years) and older children (6–<12 years). Because clearance (per kg body weight) is higher in children (<12 years), a higher dose and more frequent dosing may be needed in this population [see Clinical Pharmacology (12.3)].

Safety including immunogenicity was evaluated in 81 PUPs <6 years of age who received at least one dose of ESPEROCT [see Adverse Reactions (6.1, 6.2)].

8.5 Geriatric Use

Clinical studies of ESPEROCT did not include sufficient numbers of subjects age 65 years and over to determine whether or not they respond differently than younger subjects. Other reported clinical experience has not identified differences in responses between the elderly and younger patients. In general, dose selection for an elderly patient should be cautious, usually starting at the low end of the dosing range, reflecting the greater frequency of decreased hepatic, renal, or cardiac function, and of concomitant disease and other drug therapy.

11 DESCRIPTION

ESPEROCT is a sterile, preservative-free, non-pyrogenic lyophilized powder for intravenous injection after reconstitution with the provided saline diluent. The active ingredient in ESPEROCT is a recombinant analogue of human coagulation Factor VIII (FVIII) conjugated with a 40-kDa polyethylene glycol (PEG) molecule. ESPEROCT is formulated with the following excipients: sodium chloride, L-histidine, sucrose, polysorbate 80, L-methionine, and calcium chloride.

FVIII activity in ESPEROCT is determined using the chromogenic assay described in the European Pharmacopoeia. The activity assignment employs a FVIII reference material that is traceable to the current World Health Organization (WHO) international standard for FVIII concentrate, and evaluated by appropriate methodologies to ensure the accuracy of the results. ESPEROCT is available in single-dose vials that contain nominally 500, 1000, 1500, 2000, 3000, 4000, or 5000 IU of FVIII. Each vial of ESPEROCT is labeled with the actual FVIII activity. After reconstitution with the supplied diluent (0.9% saline), each mL of the solution contains approximately 125, 250, 375, 500, 750, 1000, or 1250 IU of FVIII, respectively.

The FVIII protein in ESPEROCT is produced in Chinese Hamster Ovary (CHO) cells using recombinant DNA technology, and contains a truncated B domain, which is O-glycosylated. The polypeptide part of the molecule has a molecular mass of 166 kDa (calculated excluding post-translational modifications) and represents a heterodimer of a heavy chain and a light chain, which are held together by non-covalent interactions. The recombinant FVIII protein is purified using a series of chromatographic steps, one of which is affinity chromatography, with the use of a monoclonal antibody to selectively isolate the rFVIII from the cell culture medium. The 40-kDa PEG molecule is conjugated to the O-glycan moiety of the B domain using an enzymatic reaction to produce a glycopegylated FVIII (FVIII-PEG). The purification process includes two viral clearance steps, namely detergent treatment for inactivation of enveloped viruses, and 20-nm filtration for removal of enveloped and non-enveloped viruses. No additives of human or animal origin are used during the manufacturing process and formulation of ESPEROCT.

In the blood circulation, when FVIII-PEG is activated by thrombin, the B-domain portion with the attached PEG moiety is cleaved off, and the resulting activated FVIII (FVIIIa) is similar in structure and function to native FVIIIa.

12 CLINICAL PHARMACOLOGY

12.1 Mechanism of Action

ESPEROCT, a glycopegylated form of recombinant anti-hemophilic factor, temporarily replaces the missing coagulation Factor VIII needed for effective hemostasis in congenital hemophilia A patients. The Factor VIII in ESPEROCT is conjugated to a 40-kDa polyethylene glycol molecule which increases the half-life and decreases the clearance compared to the non-pegylated molecule.

12.2 Pharmacodynamics

The administration of ESPEROCT increases plasma levels of Factor VIII and can temporarily correct the coagulation defect in hemophilia A patients, as reflected by a decrease in activated partial thromboplastin time (aPTT).

12.3 Pharmacokinetics

All pharmacokinetic studies with ESPEROCT were conducted in previously treated subjects with severe hemophilia A (Factor VIII<1%). In total, 129 single-dose pharmacokinetic profiles of ESPEROCT were evaluated in 86 subjects (including 24 pediatric subjects, 1 to <12 years).

Table 4 shows data for subjects who each received a single dose of 50 IU/kg. The plasma samples were analyzed using the one-stage clotting assay. There was a trend of increasing incremental recovery and AUC, and decreasing clearance, with age.

Table 4: Single-dose PK parameters of ESPEROCT 50 IU/kg, by age, using one-stage clotting assay (geometric mean (CV%))

PK Parameter No. of subjects | 1 to <6 years N=12 | 6 to <12 years N=10 | 12 to <18 years N=3 | >18 years N=42
No. of profiles | 12 | 10 | 5 | 78
IR (IU/dL) per (IU/kg)a | 1.82 (32) | 1.67 (22) | 2.45 (16) | 2.53 (24)
FVIII recovery (IU/dL)a | 103.2 (27) | 98.7 (18) | 117.7 (14) | 130.4 (26)
t1/2 (hours) | 14.7 (27) | 13.8 (32) | 17.4 (39) | 21.7 (33)
AUCinf (IU*hour/dL) | 2305 (42) | 2197 (38) | 3063 (40) | 4110 (38)
CL (mL/hour/kg) | 2.4 (42) | 2.7 (42) | 1.6 (39) | 1.2 (34)
Vss (mL/kg) | 44.2 (25) | 47.3 (28) | 36.4 (12) | 37.3 (26)
MRT (hours) | 18.1 (27) | 17.8 (35) | 23.4 (43) | 27.4 (28)b

PK parameters are presented in geometric mean.

Abbreviations: IR = Incremental recovery; t1/2 = terminal half-life; AUC = area under the FVIII activity time profile; CL = clearance; Vss = volume of distribution at steady-state; MRT = mean residence time; CV% = coefficient of variation

a IR and FVIII recovery were assessed 30 minutes post-dosing 50 IU/kg for patients ≥12 years and 60 minutes post-dosing 50 IU/kg (first sample) for children <12 years.

b Calculation based on 64 profiles.

In the single-dose PK assessment in adult subjects, whose body mass index (BMI) ranged from 17-35 kg/m^2, differences were noted for individuals who were overweight (BMI 25 - <30 kg/m^2) and obese (BMI 30 - <35 kg/m^2). Incremental recovery was increased by approximately 17% and 41%, AUC was increased by approximately 10% and 27%, and clearance was decreased by approximately 8% and 23% respectively, all in comparison to those subjects with BMI <25 kg/m^2. There is insufficient data to recommend specific dose adjustments for overweight and obese patients. The dose may be adjusted as necessary per prescriber’s discretion.

Observed pre-dose (trough) and post-dose (peak) plasma Factor VIII activity levels at steady-state during prophylactic treatment with ESPEROCT are presented in Table 5 by dose regimen and age range.

Table 5: Steady-state trough and peak plasma FVIII activity by age and dose regimen, chromogenic assay (geometric mean [95% CI])

Dose Regimen | 60 IU/kg twice weekly** (50–75 IU/kg) |  | 50 IU/kg Q4D* |  | 75 IU/kg Q7D*
Age range; No. patients | <6 years; N=31 | 6 to <12 years; N=34 | 12 to <18 years; N=23 | ≥18 years; N=143 | 12 to <18 years; N=6 | ≥18 years; N=29
Trough, IU/dL | 1.2; (0.8; 1.6) | 2.0; (1.5; 2.7) | 2.7; (1.8; 4.0) | 3.0; (2.6; 3.5) | 0.6; (0.2; 1.6) | 1.3; (0.9; 2.0)
Peak,; IU/dL | 125.0; (118.7; 131.6) | 143.3; (136.8; 150.2) | 125.1; (116.0; 135.0) | 137.9; (133.9; 142.2) | 198.0; (166.8; 235.2) | 197.9; (184.9; 212.7)

*Data included in analysis: adolescents/adults Main Phase until Visit 8 (end of the Main Phase) 50 IU/kg Q4D, and extension 1 for 75 IU/kg Q7D. Only measurements collected at steady-state for the given prophylaxis treatment are included in the analyses.

**Data included in analysis: pediatric Main Phase 60 IU/kg (50 to 75 IU/kg) twice weekly. Only measurements collected at steady-state for the given prophylaxis treatment are included in the analyses.

Time of Factor VIII Activity Above 5%

Steady-state Factor VIII activity profiles were estimated using a one-compartment model with first-order elimination with PK parameters of clearance (CL) and volume of distribution (Table 6). Pharmacokinetic predictions showed that in all age groups, patients dosed twice weekly (dosing interval alternating between 3 and 4 days) or Q4D will be above 5% Factor VIII activity (i.e., in the range of mild hemophilia) for the majority of time (72 to 95% of time). Patients dosed with 50 IU/kg every 4 days will be above 1% Factor VIII activity 100% of the dosing interval. Patients dosed with 75 IU/kg every 7 days are predicted to be above 5% for 57% of time and above 1% for 83% of time.

Table 6: Estimation of steady-state peak and trough FVIII activity and time to 5% FVIII activity for ESPEROCT

Dose regimen Age range | 60 IU/kg (50–75 IU/kg) twice weekly <12 years | 50 IU/kg twice weekly ≥12 years | 50 IU/kg Q4D ≥12 years | 75 IU/kg Q7D ≥12 years
Peak FVIII activity (%) | 110/112* | 133/138* | 132 | 194
Trough FVIII activity (%) | 2.8/0.8* | 8.6/3.6* | 3.5 | 0.3
Time to 5% FVIII activity (days) | 2.5/2.5* | 3.6/3.6* | 3.6 | 4.0
% of time in dosing interval above 5% FVIII activity | 72 | 95 | 90 | 57

*Twice weekly values are shown as 3 day/4 day. Only 50 IU/kg data are used for the analysis.

13 NONCLINICAL TOXICOLOGY

13.1 Carcinogenesis, Mutagenesis, Impairment of Fertility

Carcinogenesis, mutagenesis, and impairment of fertility studies in animals have not been performed.

13.2 Animal Toxicology and/or Pharmacology

No adverse effects were observed in immune-deficient rats intravenously injected with ESPEROCT (50-1200 IU/kg/ injection), once every 4th day for 52 weeks. No evidence of polyethylene glycol accumulation was detected by immunohistochemical staining of brain tissue, including the choroid plexus.

14 CLINICAL STUDIES

The safety and efficacy of ESPEROCT have been evaluated in five multinational, open-label trials in male subjects with severe hemophilia A (<1% endogenous Factor VIII activity). One trial was subsequently partially randomized to evaluate two different prophylaxis regimens. All subjects were previously treated, which was defined as having received other Factor VIII products for ≥150 exposure days for adolescents and adults, and ≥50 exposure days for pediatric subjects. The key exclusion criteria across trials included known or suspected hypersensitivity to trial or related products and known history of Factor VIII inhibitors or current inhibitor ≥0.6 Bethesda units (BU).

The efficacy evaluation included 254 subjects, who received at least one dose of ESPEROCT, in the following trials:

- Adolescent/adult trial: This trial included 186 subjects, 161 adults (18 to 65 years old) and 25 adolescents (12 to <18 years old); it consisted of a Main Phase and optional Extension Phase. During the Main Phase, 175 subjects received the prophylaxis regimen which consisted of 50 IU/kg every 4 days (Q4D), while 12 adults chose to be treated on-demand. (One subject changed from on-demand to prophylaxis and is counted in both groups.) Thirteen (7%) of 175 adults in the prophylaxis arm modified their dosing regimen to Q3-4D dosing for ease of use. All subjects received at least one dose of ESPEROCT and are evaluable for safety and efficacy. A total of 165 subjects (91%) completed the Main Phase of this trial.
  - Extension: This extension compared two dose regimens: 75 IU/kg every 7 days (Q7D) and 50 IU/kg Q4D. The randomization was open to subjects who experienced 2 or fewer bleeds during the last 6 months in the Main Phase.
- Pediatric trial: This trial of PTPs included 68 subjects who were evenly divided with 34 in each age group, 0 to <6 and 6 to <12 years of age. All subjects received the same prophylaxis regimen of approximately 65 IU/kg (50–75 IU/kg) twice weekly. A total of 63 subjects (93%) completed the Main Phase.
- Surgery trial: In the surgery trial, 33 previously treated adolescents/adults underwent 45 major surgeries. The dose level of ESPEROCT was chosen so that FVIII activity at least as recommended by World Federation of Hemophilia (WFH) guidelines was targeted. All subjects returned to the adolescent/adult trial after the surgery trial assessments were completed.

On-demand Treatment and Control of Bleeding Episodes

There were 1506 bleeds reported in 171 of 254 subjects across the completed clinical trials, and the most common bleed types were joint (65.2%), muscle (14.5%), and subcutaneous (8.9%). Table 7 summarizes the efficacy in control of bleeding episodes by age.

Doses used for treatment of bleeding episodes depended on age, treatment regimen and the severity of the bleed.

Of the 1407 mild and moderate bleeding episodes in all subjects in the adolescent/adult study, the median dose used was 42 IU/kg. For subjects who were on the on-demand arm the median initial dose was 28 IU/kg and 88.4% of the bleeds were treated successfully with a single dose. In subjects receiving routine prophylaxis, the median initial dose was 52 IU/kg, and 76.4% of the bleeds were successfully treated with a single dose. Of the 15 severe bleeds, 12 (80%) required more than one dose with a total median dose of 111 IU/kg.

In the pediatric study, 70 mild/moderate bleeds in children <12 years old receiving routine prophylaxis were treated with a median initial dose of 64 IU/kg per injection, with 63% treated with a single injection. When needed, additional median doses of 62 IU/kg were used at approximately 24-hour intervals. The median total dose was 70 IU/kg per bleed.

Table 7: Summary of efficacy in control of bleeding episodes by age

Age range # of subjects |  | <6 years N=34 | 6 to <12 years N=34 | 12 to <18years N=25 | ≥ 18 years N=161 | Total N=254
# of bleeds |  | 30 | 40 | 112 | 1324 | 1506
# of injections | 1 to 2 | 76.7% | 82.5% | 88.4% | 95.5% | 94.3%
# of injections | > 2 | 23.3% | 17.5% | 11.6% | 4.5% | 5.7%
Response to first treatment | Excellent/ Good | 80.0% | 77.5% | 75.0% | 88.7% | 87.3%
Response to first treatment | Moderate | 13.3% | 17.5% | 17.9% | 10.3% | 11.1 %

Definition of Hemostatic Response:

Excellent: Abrupt pain relief and/or unequivocal improvement in objective signs of bleeding within approximately 8 hours after a single injection.

Good: Definite pain relief and/or improvement in signs of bleeding within approximately 8 hours after one injection, but possibly requiring more than one injection for complete resolution.

Moderate: Probable or slight beneficial effect within approximately 8 hours after the first injection; usually requiring more than one injection.

Perioperative Management

The efficacy analysis of ESPEROCT in perioperative management included 45 major surgical procedures performed in 33 adolescent and adult subjects. The procedures included 15 joint replacements, 9 arthroscopic orthopedic interventions, 17 other orthopedic interventions, and 4 non-orthopedic surgeries.

The clinical evaluation of hemostatic response during major surgery was assessed using a 4-point scale of excellent, good, moderate, or none. The hemostatic effect of ESPEROCT was rated as “excellent” or “good” in 43 of 45 surgeries (95.6%), while the effect was rated as “moderate” in 2 surgeries (4.4%). No surgery had an outcome rated as “none” or “missing.”

The median pre-operative dose for adults and adolescents undergoing major surgeries was 52 IU/kg, and the median total dose was 702 IU/kg. During post-operative days 1-6, the median dose was 32 IU/kg at approximately 24-hour intervals. During post-operative days 7-14, the median dose was 36 IU/kg at approximately 28-hour intervals. The number of doses and duration of treatment varied by procedure.

Routine Prophylaxis in Adolescents/Adults

The efficacy of ESPEROCT in routine prophylaxis with Q4D dosing was demonstrated for the adult/adolescent population (see Table 8). In the extension part of the study, treatment success of the Q7D arm was not established. During the Main Phase of the adolescent/adult trial, 186 subjects had a total of 159 exposure years. The median annualized bleeding rate (ABR) for treated bleeds in adults and adolescents treated every 4 days was 1.2 (IQR: 0.0:4.3), and mean ABR was 3.0 (SD: 4.7). When including all bleeds (treated and non-treated), the median ABR was 1.2 (IQR: 0.0; 4.7) and the mean ABR was 3.3 (SD: 4.9).

Table 8: Efficacy in adolescent/adult prophylaxis, median and mean ABRs by age, treatment regimen, and bleed type

 | Prophylaxis |  |  | On-demand
Age Range | 12 to 17 years | 18 to 70 years | 12 to 70 years | 18 to 70 years
# of subjects | 25 | 150 | 175 | 12
Mean treatment duration (years) | 0.85 | 0.81 | 0.82 | 1.33
Treated bleeds; # of subjects with bleeds (%); # of subjects without bleeds (%); # of bleeds; Median ABR (IQR); Mean ABR (SD) | 19 (76); 6 (24); 67; 2.2 (0.9;4.7); 3.5 (3.9) | 86 (57); 64 (43); 369; 1.2 (0.0;3.7); 2.9 (4.8) | 105 (60); 70 (40); 436; 1.2 (0.0;4.3); 3.0 (4.7) | 12 (100); 0; 532; 30.9 (18.6;38.5); 31.9 (19.1)
All bleeds (treated and untreated); # of subjects with bleeds (%); # of subjects without bleeds (%); # of bleeds*; Median ABR (IQR); Mean ABR (SD) | 19 (76); 6 (24); 72; 2.2 (0.9;6.0); 3.7 (4.1) | 88 (59); 62 (41); 386; 1.2 (0.0;4.3); 3.2 (5.1) | 107 (61); 68 (39); 458; 1.2 (0.0;4.7); 3.3 (4.9) | 12 (100); 0; 536; 31.3 (18.6;38.9); 32.2 (19.1)
Treated spontaneous bleeds; # of subjects with bleeds (%); # of subjects without bleeds (%) # of bleeds; Median AsBR (IQR); Mean AsBR (SD) | 11 (44); 14 (56); 30; 0.0 (0.0;1.5); 1.4 (2.4) | 65 (43); 85 (57); 221; 0.0 (0.0;1.9); 1.8 (3.7) | 76 (43); 99 (57) 251; 0.0 (0.0;1.8); 1.7 (3.5) | 12 (100); 0; 415; 19.4 (12.1;31.0); 24.5 (17.3)
Treated traumatic bleeds # of subjects with bleeds (%); # of subjects without bleeds (%); # of bleeds Median AtBR (IQR); Mean AtBR (SD) | 16 (64); 9 (36); 37; 1.3 (0.0;2.6); 2.1 (2.9) | 57 (38); 93 (62); 146; 0.0 (0.0;1.4); 1.1 (2.2) | 73 (42); 102 (58); 183 0.0 (0.0;1.7); 1.2 (2.3) | 10 (83); 2 (17); 110 4.3 (0.8;9.9); 6.1 (6.2)
Treated joint bleeds # of subjects with bleeds (%); # of subjects without bleeds (%); # of bleeds Median AjBR (IQR); Mean AjBR (SD) | 16 (64); 9 (36); 37; 1.2 (0.0;2.8); 1.8 (2.2) | 74 (49); 76 (51); 288; 0.0 (0.0;2.8); 2.3 (4.3) | 90 (51); 85 (49); 325; 0.9 (0.0;2.8); 2.2 (4.1) | 12 (100); 0; 309 19.4 (4.5;28.8); 19.7 (15.1)

ABR = annualized bleed rate; IQR = interquartile range, 25th percentile to 75th percentile; SD = standard deviation; AsBR = annualized spontaneous bleed rate; AtBR = annualized traumatic bleed rate; AjBR = annualized joint bleed rate.

*Reflects all bleeds reported by patients including those where no ESPEROCT was administered

Routine Prophylaxis in Children <12 Years of Age

Overall, 68 children below 12 years received prophylactic treatment with ESPEROCT at an average dose of approximately 65 IU/kg twice weekly. The prophylactic effect of ESPEROCT was demonstrated with a median ABR rate of 2.0 (IQR: 0.0; 2.8) and 2.0 (IQR: 0.0; 4.2) for treated bleeds and all bleeds respectively (see Table 9). The mean ABR (SD) for treated bleeds and all bleeds were 3.1 (7.1) and 4.4 (8.7), respectively. Of the 68 children, 22 (32%) did not experience any bleeding episodes and 29 (43%) did not experience any bleeding episodes that required treatment during the Main Phase of the trial. Of the 13 subjects with 17 documented target joints at baseline, 10 subjects (77%) and 14 target joints (82%) did not have any bleeds during the Main Phase of the trial.

Table 9: Efficacy in pediatric prophylaxis, median and mean ABR by age and bleed type

 | Prophylaxis Regimen
Age range | < 6 years** | 6 to < 12 years | 0 to < 12 years
# of subjects | N=34 | N=34 | N=68
Mean treatment duration (years) | 0.46 | 0.51 | 0.48
Treated bleeds; # of subjects with bleeds (%); # of subjects without bleeds (%); # of bleeds; Median ABR (IQR); Mean ABR (SD) | 19 (56); 15 (44); 30; 1.9 (0.0;2.1); 3.9 (9.7) | 20 (59); 14 (41); 40; 2.0 (0.0;3.9); 2.3 (2.9) | 39 (57); 29 (43); 70; 2.0 (0.0;2.8); 3.1 (7.1)
All Bleeds (treated and untreated); # of subjects with bleeds (%); # of subjects without bleeds (%); # of bleeds*; Median ABR (IQR); Mean ABR (SD) | 20 (59); 14 (41); 41; 2.0 (0.0;4.0); 5.0 (11.9) | 26 (77); 8 (24); 65; 2.0 (1.9;6.0); 3.8 (3.6) | 46 (68); 22 (32); 106; 2.0 (0.0;4.2); 4.4 (8.7)
Treated spontaneous bleeds; # of subjects with bleeds (%); # of subjects without bleeds (%); # of bleeds; Median AsBR (IQR); Mean AsBR (SD) | 6 (18); 28 (82); 9; 0.0 (0.0;0.0); 2.1 (7.3) | 7 (21); 27 (79); 10; 0.0 (0.0; 0.0); 0.6 (1.5) | 13 (19); 55 (81); 19; 0.0 (0.0; 0.0); 1.3 (5.3)
Treated traumatic bleeds; # of subjects with bleeds (%); # of subjects without bleeds (%); # of bleeds; Median AtBR (IQR); Mean AtBR (SD) | 15 (44); 19 (56); 20; 0.0 (0.0; 2.0); 1.7 (4.0) | 17 (50); 17 (50); 30; 0.9 (0.0;2.0); 1.7 (2.5) | 32 (47); 36 (53); 50; 0.0 (0.0;2.0); 1.7 (3.3)
Treated joint bleeds; # of subjects with bleeds (%); # of subjects without bleeds (%); # of bleeds; Median AjBR (IQR); Mean AjBR (SD) | 7 (21); 27 (79); 10; 0.0 (0.0;0.0); 1.5 (6.3) | 12 (35); 22 (65); 24; 0.0 (0.0;2.0); 1.4 (2.4) | 19 (28); 49 (72); 34; 0.0 (0.0;2.0); 1.5 (4.7)

ABR = annualized bleed rate; IQR = interquartile range, 25th percentile to 75th percentile; SD = standard deviation; AsBR = annualized spontaneous bleed rate; AtBR = annualized traumatic bleed rate; AjBR = annualized joint bleed rate

*Reflects all bleeds reported by patients including those where no ESPEROCT was administered

**Elevated mean ABRs are due to subjects who withdrew from the study, whose bleeding rates were extrapolated to one year

16 HOW SUPPLIED/STORAGE AND HANDLING

How Supplied

- ESPEROCT is supplied in packages comprised of a single-dose vial containing nominally 500, 1000, 1500, 2000, 3000, 4000, or 5000 IU of Factor VIII activity; a MixPro® pre-filled diluent syringe containing 0.9% saline solution; and a sterile vial adapter with a 25-micrometer filter, which serves as a needleless reconstitution device.
- The actual Factor VIII activity in IU is stated on each ESPEROCT carton and vial label.

Table 10: ESPEROCT Presentations

Nominal Dosage Strength | Cap Color Indicator | Carton NDC Number | Components
500 IU | Red | NDC 0169 8500 01 | - ESPEROCT in single-dose vial [NDC 0169 8501 11] - Pre-filled syringe with 4 mL sterile saline diluent [NDC 0169 8008 98] - Vial adapter
1000 IU | Green | NDC 0169 8100 01 | - ESPEROCT in single-dose vial [NDC 0169 8101 11] - Pre-filled syringe with 4 mL sterile saline diluent [NDC 0169 8008 98] - Vial adapter
1500 IU | Gray | NDC 0169 8150 01 | - ESPEROCT in single-dose vial [NDC 0169 8151 11] - Pre-filled syringe with 4 mL sterile saline diluent [NDC 0169 8008 98] - Vial adapter
2000 IU | Yellow | NDC 0169 8200 01 | - ESPEROCT in single-dose vial [NDC 0169 8201 11] - Pre-filled syringe with 4 mL sterile saline diluent [NDC 0169 8008 98] - Vial adapter
3000 IU | Black | NDC 0169 8300 01 | - ESPEROCT in single-dose vial [NDC 0169 8301 11] - Pre-filled syringe with 4 mL sterile saline diluent [NDC 0169 8008 98] - Vial adapter
4000 IU | Light Pink | NDC 0169 8400 01 | - ESPEROCT in single-dose vial [NDC 0169 8401 11] - Pre-filled syringe with 4 mL sterile saline diluent [NDC 0169 8008 98] - Vial adapter
5000 IU | Dark Blue | NDC 0169 8055 01 | - ESPEROCT in single-dose vial [NDC 0169 8051 11] - Pre-filled syringe with 4 mL sterile saline diluent [NDC 0169 8008 98] - Vial adapter

IU = International Units

- The ESPEROCT vials are made of glass, closed with a chlorobutyl rubber stopper (not made with natural rubber latex), and sealed with an aluminum cap.
- The pre-filled diluent syringes are made of glass with a siliconized bromobutyl rubber plunger (not made with rubber latex).
- The closed vials and pre-filled diluent syringes are equipped with a tamper-evident snap-off cap which is made of polypropylene.

Storage and Handling

- Store ESPEROCT in the original package to protect the ESPEROCT vial from light.
- Store ESPEROCT in a powder form under refrigeration at 36°F to 46°F (2°C to 8°C) for up to 30 months from the date of manufacture until the expiration date stated on the label. During the 30-month shelf life, ESPEROCT may be kept at room temperature:
  - up to 86°F (30°C) for no longer than 12 months, or
  - up to 104°F (40°C) for no longer than 3 months
- Record the date on the carton when the product was removed from the refrigerator. Do not return the product to the refrigerator.
- Do not freeze ESPEROCT.
- Use ESPEROCT within 4 hours after reconstitution when stored at ≤86°F (30°C) or within 24 hours when stored in the refrigerator. Store the reconstituted product in the vial.
- Discard any unused reconstituted product.

17 PATIENT COUNSELING INFORMATION

Advise patients:

- To read the FDA-approved patient labeling (Patient Information and Instructions for Use).
- That allergic-type hypersensitivity reactions or anaphylaxis are possible with use of ESPEROCT. Inform patients of the early signs of hypersensitivity reactions including rash, hives, itching, facial swelling, tightness of the chest, and wheezing. Advise patients to discontinue use of ESPEROCT immediately and contact their healthcare provider and/or seek emergency care promptly if these symptoms occur.
- To contact their healthcare provider or treatment facility for further treatment and/or assessment if they experience a lack of a clinical response to Factor VIII replacement therapy, as this may be a manifestation of an inhibitor.

Version: 5

License Number: 1261

ESPEROCT® and MixPro® are registered trademarks of Novo Nordisk Health Care AG.

Patent Information: http://novonordisk-us.com/products/product-patents.html

Clave® and MicroClave® are registered trademarks of ICU Medical Inc.

InVision-Plus®, InVision-Plus CS®, Invision-Plus® Junior® are registered trademarks of RyMed Technologies, Inc. Bionector® is a registered trademark of Vygon.

© 2024 Novo Nordisk

For information contact:

Novo Nordisk Inc.

800 Scudders Mill Road

Plainsboro, NJ 08536, USA

1-800-727-6500

Manufactured by:

Novo Nordisk A/S

Novo Allé, DK-2880 Bagsvaerd

PATIENT PACKAGE INSERT

PATIENT INFORMATION

ESPEROCT® (es’per okt)

[antihemophilic factor (recombinant), glycopegylated-exei]

Read the Patient Information and the Instructions for Use that come with ESPEROCT before you start taking this medicine and each time you get a refill. There may be new information.

This Patient Information does not take the place of talking with your healthcare provider about your medical condition or treatment. If you have questions about ESPEROCT after reading this information, ask your healthcare provider.

What is the most important information I need to know about ESPEROCT?

Do not attempt to do an infusion yourself unless you have been taught how by your healthcare provider or hemophilia treatment center.

You must carefully follow your healthcare provider's instructions regarding the dose and schedule for infusing ESPEROCT so that your treatment will work best for you.

What is ESPEROCT?

ESPEROCT is an injectable medicine used to replace clotting Factor VIII that is missing in patients with hemophilia A. Hemophilia A is an inherited bleeding disorder in all age groups that prevents blood from clotting normally.

ESPEROCT is used to treat and prevent or reduce the number of bleeding episodes in people with hemophilia A.

Your healthcare provider may give you ESPEROCT when you have surgery.

Who should not use ESPEROCT?

You should not use ESPEROCT if you

- are allergic to Factor VIII or any of the other ingredients of ESPEROCT
- if you are allergic to hamster proteins

If you are not sure, talk to your healthcare provider before using this medicine.

Tell your healthcare provider if you are pregnant or nursing because ESPEROCT might not be right for you.

What should I tell my healthcare provider before I use ESPEROCT?

You should tell your healthcare provider if you:

- Have or have had any medical conditions.
- Take any medicines, including non-prescription medicines and dietary supplements.
- Are nursing.
- Are pregnant or planning to become pregnant.
- Have been told that you have inhibitors to Factor VIII.

How should I use ESPEROCT?

Treatment with ESPEROCT should be started by a healthcare provider who is experienced in the care of patients with hemophilia A.

ESPEROCT is given as an infusion into the vein.

You may infuse ESPEROCT at a hemophilia treatment center, at your healthcare provider's office or in your home. You should be trained on how to do infusions by your hemophilia treatment center or healthcare provider. Many people with hemophilia A learn to infuse the medicine by themselves or with the help of a family member.

Your healthcare provider will tell you how much ESPEROCT to use based on your weight, the severity of your hemophilia A, and where you are bleeding. Your dose will be calculated in international units, IU.

Call your healthcare provider right away if your bleeding does not stop after taking ESPEROCT.

If your bleeding is not adequately controlled, it could be due to the development of Factor VIII inhibitors. This should be checked by your healthcare provider. You might need a higher dose of ESPEROCT or even a different product to control bleeding. Do not increase the total dose of ESPEROCT to control your bleeding without consulting your healthcare provider.

Use in children

ESPEROCT can be used in children. Your healthcare provider will decide the dose of ESPEROCT you will receive.

If you forget to use ESPEROCT

If you forget a dose, infuse the missed dose when you discover the mistake. Do not infuse a double dose to make up for a forgotten dose. Proceed with the next infusions as scheduled and continue as advised by your healthcare provider.

If you stop using ESPEROCT

Do not stop using ESPEROCT without consulting your healthcare provider.

If you have any further questions on the use of this product, ask your healthcare provider.

What if I take too much ESPEROCT?

Always take ESPEROCT exactly as your healthcare provider has told you. You should check with your healthcare provider if you are not sure. If you infuse more ESPEROCT than recommended, tell your healthcare provider as soon as possible.

What are the possible side effects of ESPEROCT?

Common Side Effects Include:

- rash or itching
- swelling, pain, rash or redness at the location of infusion

Other Possible Side Effects:

You could have an allergic reaction to coagulation Factor VIII products. Call your healthcare provider right away or get emergency treatment right away if you get any signs of an allergic reaction, such as: hives, chest tightness, wheezing, dizziness, difficulty breathing, and/or swelling of the face.

Your body can also make antibodies called “inhibitors” against ESPEROCT, which may stop ESPEROCT from working properly. Your healthcare provider may need to test your blood for inhibitors from time to time.

These are not all of the possible side effects from ESPEROCT. Ask your healthcare provider for more information. You are encouraged to report side effects to FDA at 1-800-FDA-1088.

Tell your healthcare provider about any side effect that bothers you or that does not go away.

What are the ESPEROCT dosage strengths?

ESPEROCT comes in seven different dosage strengths. The actual number of international units (IU) of Factor VIII in the vial will be imprinted on the label and on the box. The seven different strengths are as follows:

Cap Color Indicator | Nominal Strength
Red | 500 IU per vial
Green | 1000 IU per vial
Gray | 1500 IU per vial
Yellow | 2000 IU per vial
Black | 3000 IU per vial
Light Pink | 4000 IU per vial
Dark Blue | 5000 IU per vial

Always check the actual dosage strength printed on the label to make sure you are using the strength prescribed by your healthcare provider.

How should I store ESPEROCT?

Prior to Reconstitution (mixing the dry powder in the vial with the diluent):

Protect from light. Do not freeze ESPEROCT.

ESPEROCT can be stored in refrigeration at 36°F to 46°F (2°C to 8°C) for up to 30 months until the expiration date stated on the label. During the 30-month shelf life, ESPEROCT may be kept at room temperature, not to exceed 86°F (30°C) for up to 12 months, or up to 104°F (40°C) for no longer than 3 months.

If you choose to store ESPEROCT at room temperature:

- Record the date when the product was removed from the refrigerator.
- Do not return the product to the refrigerator.
- Do not use after 12 months if stored up to 86°F (30°C) or after 3 months if stored up to 104°F (40°C) or the expiration date listed on the vial, whichever is earlier.

Do not use this medicine after the expiration date which is on the outer carton and the vial. The expiration date refers to the last day of that month.

After Reconstitution:

The reconstituted (the final product once the powder is mixed with the diluent) ESPEROCT should appear clear and colorless without visible particles.

The reconstituted ESPEROCT should be used immediately.

If you cannot use the reconstituted ESPEROCT immediately, it must be used within 4 hours when stored at or below 86ºF (30°C) or within 24 hours when stored in a refrigerator at 36°F to 46°F (2°C to 8°C). Store the reconstituted product in the vial.

Keep this medicine out of the sight and out of reach of children.

What else should I know about ESPEROCT and hemophilia A?

Medicines are sometimes prescribed for purposes other than those listed here. Do not use ESPEROCT for a condition for which it is not prescribed. Do not share ESPEROCT with other people, even if they have the same symptoms that you have.

For more information about ESPEROCT, please call Novo Nordisk at 1-800-727-6500.

What are the ingredients in ESPEROCT?

Active ingredients: recombinant analogue of human coagulation Factor VIII (FVIII) conjugated with a 40-kDa polyethylene glycol (PEG) molecule

Inactive ingredients: sodium chloride, L-histidine, sucrose, polysorbate 80, L-methionine, and calcium chloride

ESPEROCT® is a trademark of Novo Nordisk Health Care AG.

For Patent Information, refer to: http://novonordisk-us.com/products/product-patents.html.

© 2024 Novo Nordisk

Manufactured by: Novo Nordisk A/S, Novo Allé DK-2880 Bagsvaerd, Denmark

For information about ESPEROCT contact:

Novo Nordisk Inc., 800 Scudders Mill Road, Plainsboro, NJ 08536, USA

This Patient Information has been approved by the U.S. Food and Drug Administration. Revised: 07/2024

Instructions for Use

Instructions on how to use ESPEROCT® [antihemophilic factor (recombinant), glycopegylated-exei] MixPro®

READ THESE INSTRUCTIONS CAREFULLY BEFORE USING ESPEROCT.

ESPEROCT is supplied as a powder. Before infusion (administration) it must be mixed (reconstituted) with the liquid diluent supplied in the syringe. The liquid diluent is a sodium chloride solution. The mixed ESPEROCT must be infused into your vein (intravenous infusion). The equipment in this package is designed to mix and infuse ESPEROCT.

You will also need an infusion set (butterfly needle with tubing), sterile alcohol swabs, gauze pads, and bandages.

Don’t use the equipment without proper training from your doctor or nurse.

Always wash your hands and ensure that the area around you is clean.

When you prepare and infuse medication directly into the veins, it is important to use a clean and germ free (aseptic) technique. Improper technique can introduce germs that can infect the blood.

Don’t open the equipment until you are ready to use it.

Don’t use the equipment if it has been dropped, or if it is damaged. Use a new package instead.

Don’t use the equipment if it is expired. Use a new package instead.The expiration date is printed on the outer carton and on the vial, the vial adapter and the pre-filled syringe.

Don’t use the equipment if you suspect it is contaminated. Use a new package instead.

Don’t dispose of any of the items until after you have infused the mixed solution.

The equipment is for single use only.

Single-dose container. Discard unused portion.

Content

The package contains:

• Vial with ESPEROCT powder

• Vial adapter

• Pre-filled syringe with diluent

• Plunger rod (placed under the syringe)

1. Prepare the vial and the syringe

- Take out the number of ESPEROCT packages you need.
- Check the expiry date.
- Check the name, strength and color of the package, to make sure it contains the correct product.
- Wash your hands and dry them properly using a clean towel or air dry.
- Take the vial, the vial adapter and the pre-filled syringe out of the carton. Leave the plunger rod untouched in the carton.
- Bring the vial and the pre-filled syringe to room temperature. You can do this by holding them in your hands until they feel as warm as your hands.

- Remove the plastic cap from the vial. If the plastic cap is loose or missing, don’t use the vial.
- Wipe the rubber stopper with a sterile alcohol swab and allow it to air dry for a few seconds before use to ensure that it is as germ free as possible.
- Don’t touch the rubber stopper with your fingers as this can transfergerms.

2. Attach the vial adapter

- Remove the protective paper from the vial adapter.
Don’t take the vial adapter out of the protective cap with your fingers. If you touch the spike on the vial adapter germs from your fingers can be transferred.
If the protective paper is not fully sealed or if it is broken, don’t use the vial adapter.

- Place the vial on a flat and solid surface.
- Turn over the protective cap, and snap the vial adapter onto the vial.
Once attached, don’t remove the vial adapter from the vial.

- Carefully remove the protective cap from the vial adapter.
Don’t lift the vial adapter from the vial when removing the protective cap.

3. Attach the plunger rod and the syringe

- Grasp the plunger rod by the wide top end and take it out of the carton. Don’t touch the sides or the thread of the plunger rod. If you touch the sides or the thread germs from your fingers can be transferred.
- Immediately connect the plunger rod to the syringe by turning it clockwise into the rubber plunger inside the pre-filled syringe until resistance is felt.

- Remove the syringe cap from the pre-filled syringe by bending it down until the perforation breaks.
Don’t touch the syringe tip under the syringe cap. If you touch the syringe tip germs from your fingers can be transferred.
If the syringe cap is loose or missing, don’t use the pre-filled syringe.

- Screw the pre-filled syringe securely onto the vial adapter until resistance is felt.

4. Mix the powder with the diluent

- Hold the pre-filled syringe slightly tilted with the vial pointing downwards.
- Push the plunger rod to inject all the diluent into the vial.

- Keep the plunger rod pressed down and swirl the vial gently until all the powder is dissolved.
Don’t shake the vial as this will cause foaming.
- Check the mixed solution. It must be clear and colorless. If you notice visible particles or discoloration, don’t use it. Use a new package instead.

ESPEROCT is recommended to be used immediately after it is mixed.

If you cannot use the mixed ESPEROCT solution immediately, it must be used within 4 hours when stored at ≤86°F (30°C) or within 24 hours when stored in a refrigerator at 36°F to 46°F (2°C to 8°C). Store the reconstituted product in the vial.

Do not freeze mixed ESPEROCT solution or store it in syringes.

Keep reconstituted ESPEROCT solution out of direct light.

If your dose requires more than one vial, repeat step A to J with additional vials, vial adapters and pre-filled syringes until you have reached your required dose.

- Keep the plunger rod pushed completely in.
- Turn the syringe with the vial upside down.
- Stop pushing the plunger rod and let it move back on its own while the mixed solution fills the syringe.
- Pull the plunger rod slightly downwards to draw the mixed solution into the syringe.
- In case you only need part of the entire vial, use the scale on the syringe to see how much mixed solution you withdraw, as instructed by your doctor or nurse.
- While holding the vial upside down, tap the syringe gently to let any air bubbles rise to the top.
- Push the plunger rod slowly until all air bubbles are gone.

- Unscrew the vial adapter with the vial.

Don’t touch the syringe tip. If you touch the syringe tip germs from your fingers can be transferred.

Caution: The pre-filled diluent syringe is made of glass with an internal tip diameter of 0.037 inches, and is compatible with a standard Luer-lock connector.

Some needleless connectors for intravenous catheters are incompatible with the glass diluent syringes (for example, certain connectors with an internal spike, such as Clave® /MicroClave®, InVision-Plus®, InVision-Plus CS®, Invision-Plus® Junior®, Bionector®).

To administer ESPEROCT through incompatible needleless connectors, withdraw reconstituted product into a standard 10 mL sterile Luer-lock plastic syringe.

If you have encountered any problems with attaching the pre-filled sodium chloride syringe to any Luer‐lock compatible device, please contact Novo Nordisk at (800) 727-6500.

5. Infuse the mixed solution

ESPEROCT is now ready to infuse into your vein.

- Do not mix ESPEROCT with any other intravenous infusions or medications.
- Infuse the mixed solution slowly over 1 to 3 minutes as instructed by your doctor or nurse.

Infusing the solution via a central venous access device (CVAD) such as a central venous catheter or subcutaneous port:

- Use a clean and germ free (aseptic) technique. Follow the instructions for proper use for your connector and central venous access device in consultation with your doctor or nurse.
- Infusing into a CVAD may require using a sterile 10 mL plastic syringe for withdrawal of the mixed solution and infusion.
- If necessary, use 0.9% Sodium Chloride Injection, USP to flush the CVAD line before or after ESPEROCT infusion.

The peel-off label found on the ESPEROCT vial can be used to record the lot number.

Disposal

- After infusion, safely dispose of all unused ESPEROCT solution, the syringe with the infusion set, the vial with the vial adapter, and other waste materials in an appropriate container for throwing away medical waste.

Don’t throw it out with the ordinary household trash.

Don’t disassemble the vial and vial adapter before disposal.

Don’t reuse the equipment.

Important information

Contact your healthcare provider or local hemophilia treatment center if you experience any problems.

For full Prescribing Information please read the other insert included in this package.

ESPEROCT® and MixPro® are trademarks of Novo Nordisk Health Care AG.

For Patent Information, refer to: http://novonordisk-us.com/patients/products/product-patents.html

© 2019 Novo Nordisk

Manufactured by:

Novo Nordisk A/S

DK-2880 Bagsvaerd, Denmark

For information about ESPEROCT contact:

Novo Nordisk Inc.

800 Scudders Mill Road

Plainsboro, NJ 08536, USA

License No: 1261

Revised: 10/2019

PACKAGE/LABEL PRINCIPAL DISPLAY PANEL

500 IU Carton

NDC 0169 8500 01 List: 850001

ESPEROCT®500 IU Range

[antihemophilic factor (recombinant), glycopegylated-exei]

500 IU

Intravenous use, after reconstitution.

Single-dose. Discard unused portion

Contains no preservatives.

Rx Only

Includes MixPro®

a vial adapter and pre-filled diluent syringe

1000 IU Carton

NDC 0169 8100 01 List: 810001

ESPEROCT®1000 IU Range

[antihemophilic factor (recombinant), glycopegylated-exei]

1000 IU

Intravenous use, after reconstitution.

Single-dose. Discard unused portion

Contains no preservatives.

Rx Only

Includes MixPro®

a vial adapter and pre-filled diluent syringe

1500 IU Carton

NDC 0169 8150 01 List: 815001

ESPEROCT®1500 IU Range

[antihemophilic factor (recombinant), glycopegylated-exei]

1500 IU

Intravenous use, after reconstitution.

Single-dose. Discard unused portion

Contains no preservatives.

Rx Only

Includes MixPro®

a vial adapter and pre-filled diluent syringe

2000 IU Carton

NDC 0169 8200 01

List: 820001

ESPEROCT®2000 IU Range

[antihemophilic factor (recombinant), glycopegylated-exei]

2000 IU

Intravenous use, after reconstitution.

Single-dose. Discard unused portion

Contains no preservatives.

Rx Only

Includes MixPro®

a vial adapter and pre-filled diluent syringe

3000 IU Carton

NDC 0169 8300 01

List: 830001

ESPEROCT®3000 IU Range

[antihemophilic factor (recombinant), glycopegylated-exei]

3000 IU

Intravenous use, after reconstitution.

Single-dose. Discard unused portion

Contains no preservatives.

Rx Only

Includes MixPro®

a vial adapter and pre-filled diluent syringe

4000 IU Carton

NDC 0169-8400-01 List: 840001

ESPEROCT®

4000 IU Range

[antihemophilic factor
(recombinant), glycopegylated-exei]
4000 IU

Intravenous use, after reconstitution.
  Single-dose. Discard unused portion.
  Contains no preservatives. Rx Only

Includes MixPro®
a vial adapter and pre-filled diluent syringe

5000 IU Carton

NDC 0169-8055-01 List: 805501

ESPEROCT®

5000 IU Range

[antihemophilic factor
(recombinant), glycopegylated-exei]

5000 IU

Intravenous use, after reconsitution.
  Single-dose. Discard unused portion.
  Contains no preservatives. Rx Only

Includes MixPro®
a vial adapter and pre-filled diluent syringe